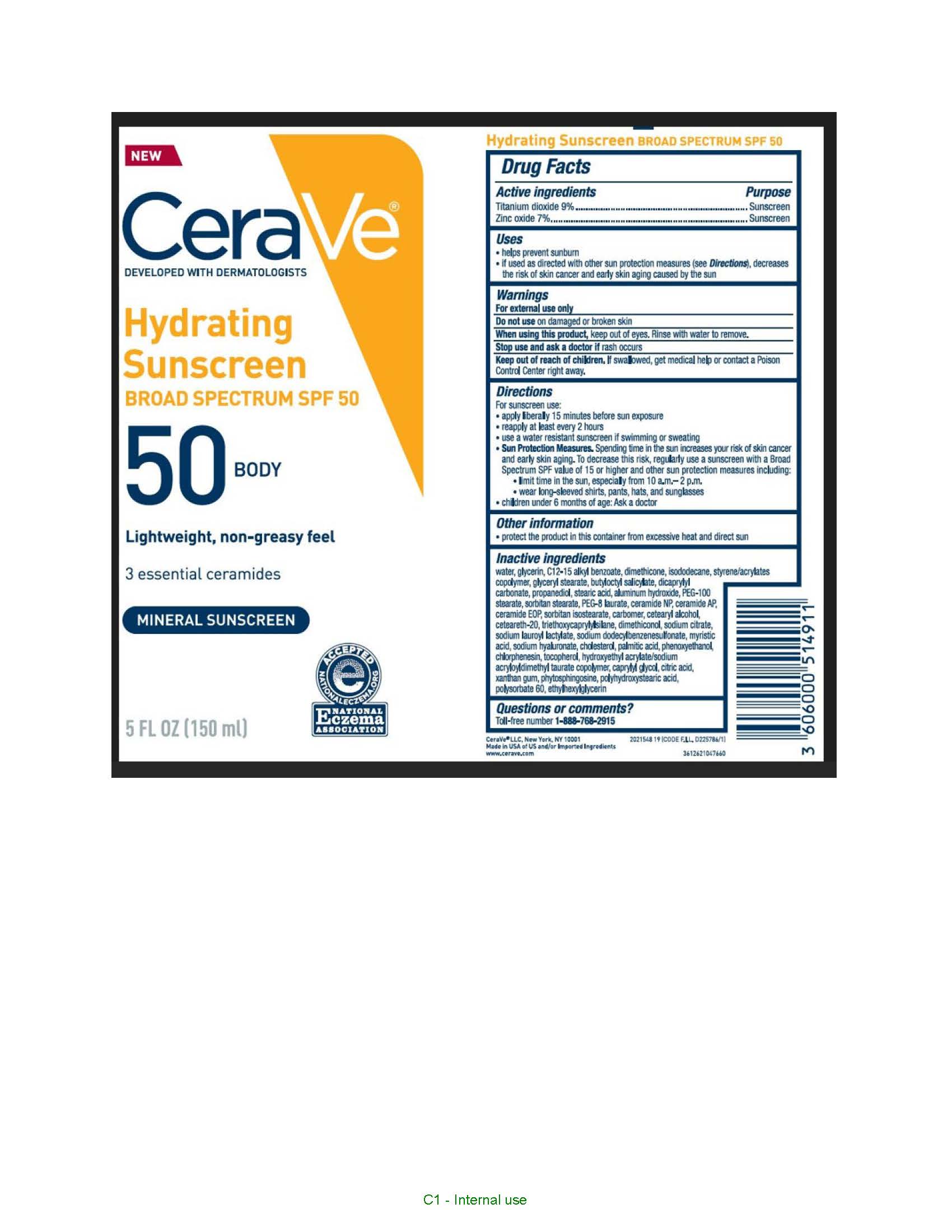 DRUG LABEL: Cerave Developed with Dermatologists Hydrating Sunscreen SPF 50 Body Lightweight, non-greasy feel 3 essential ceramides Mineral Sunscreen
NDC: 49967-911 | Form: LOTION
Manufacturer: L'Oreal USA Products Inc
Category: otc | Type: HUMAN OTC DRUG LABEL
Date: 20240116

ACTIVE INGREDIENTS: TITANIUM DIOXIDE 90 mg/1 mL; ZINC OXIDE 70 mg/1 mL
INACTIVE INGREDIENTS: WATER; GLYCERIN; ALKYL (C12-15) BENZOATE; DIMETHICONE; GLYCERYL MONOSTEARATE; ISODODECANE; BUTYLOCTYL SALICYLATE; DICAPRYLYL CARBONATE; PROPANEDIOL; STEARIC ACID; ALUMINUM HYDROXIDE; PEG-100 STEARATE; SORBITAN MONOSTEARATE; PEG-8 LAURATE; CERAMIDE NP; CERAMIDE AP; CERAMIDE 1; SORBITAN ISOSTEARATE; CARBOXYPOLYMETHYLENE; CETOSTEARYL ALCOHOL; POLYOXYL 20 CETOSTEARYL ETHER; TRIETHOXYCAPRYLYLSILANE; SODIUM CITRATE; SODIUM LAUROYL LACTYLATE; SODIUM DODECYLBENZENESULFONATE; MYRISTIC ACID; HYALURONATE SODIUM; CHOLESTEROL; PALMITIC ACID; PHENOXYETHANOL; CHLORPHENESIN; TOCOPHEROL; HYDROXYETHYL ACRYLATE/SODIUM ACRYLOYLDIMETHYL TAURATE COPOLYMER (45000 MPA.S AT 1%); CAPRYLYL GLYCOL; CITRIC ACID MONOHYDRATE; XANTHAN GUM; PHYTOSPHINGOSINE; POLYHYDROXYSTEARIC ACID (2300 MW); POLYSORBATE 60; ETHYLHEXYLGLYCERIN

Drug Facts

Active ingredients

Titanium dioxide 9%

Zinc oxide 7%

Purpose

Sunscreen

Uses

• Helps prevent sunburn
• If used as directed with other sun protection measures (see Directions), decreases the risk of skin cancer and early skin aging caused by the sun

Warnings

For external use only

Do not use

on damaged or broken skin

When using this product,

keep out of eyes. Rinse with water to remove.

Stop use and ask a doctor if

rash occurs

Keep out of reach of children.

If swallowed, get medical help or contact a Poison Control Center right away.

Directions

For sunscreen use:
• apply liberally 15 minutes before sun exposure
• reapply at least every 2 hours
• use a water resistant sunscreen if swimming or sweating
• Sun Protection Measures. Spending time in the sun increases your risk of skin cancer and early skin aging. To decrease this risk, regularly use a sunscreen with a Broad Spectrum SPF value of 15 or higher and other sun protection measures including:
o limit time in the sun, especially from 10 a.m. – 2 p.m.
o wear long-sleeved shirts, pants, hats, and sunglasses
• children under 6 months of age: Ask a doctor

Other information

• protect the product in this container from excessive heat and direct sun

Inactive ingredients

water, glycerin, C12-15 alkyl benzoate, dimethicone, isododecane, styrene/acrylates copolymer, glyceryl stearate, butyloctyl salicylate, dicaprylyl carbonate, propanediol, stearic acid, aluminum hydroxide, PEG-100 stearate, sorbitan stearate, PEG-8 laurate, ceramide NP, ceramide AP, ceramide EOP, sorbitan isostearate, carbomer, cetearyl alcohol, cetearth-20, triethoxycaprylylsilane, dimethiconol, sodium citrate, sodium lauroyl lactylate, sodium dodecylbenzenesulfonate, myristic acid, sodium hyaluronate, cholesterol, palmitic acid, phenoxyethanol, chlorphenesin, tocopherol, hydroxyethyl acrylate/sodium acryloyldimethyl taurate copolymer, caprylyl glycol, citric acid, xanthan gum, phytosphinfosine, polyhydroxystearic acid, polysorbate 60, ethylhexylglycerin

Questions or comments?

Toll-free number 1-888-768-2915